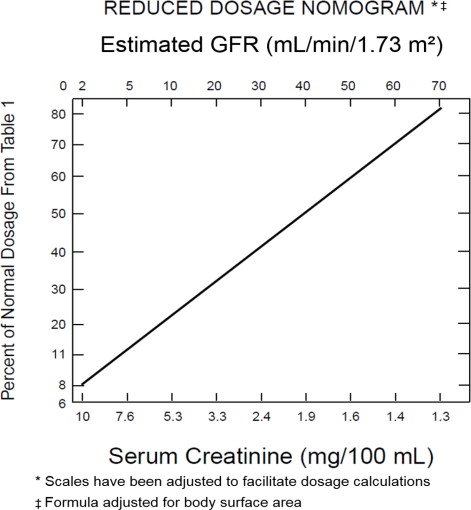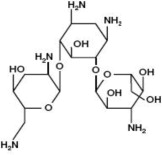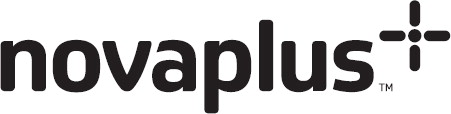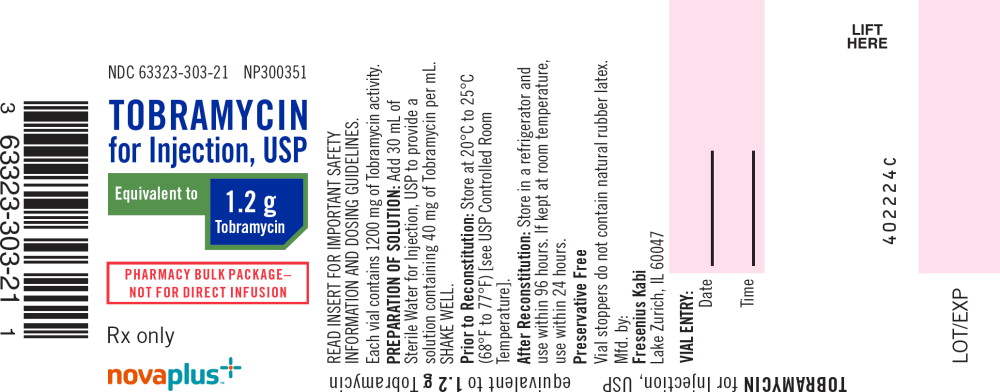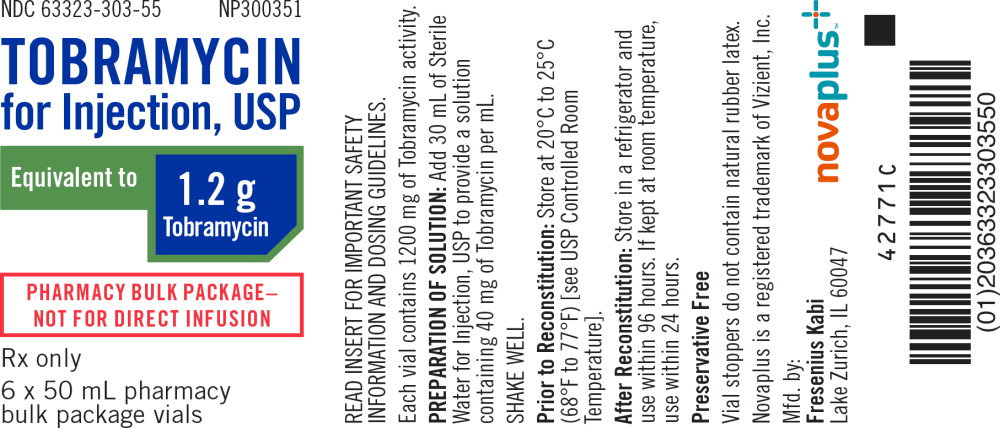 DRUG LABEL: Tobramycin

NDC: 63323-303 | Form: INJECTION, POWDER, FOR SOLUTION
Manufacturer: Fresenius Kabi USA, LLC

Category: prescription | Type: HUMAN PRESCRIPTION DRUG LABEL
Date: 20240207

ACTIVE INGREDIENTS: TOBRAMYCIN SULFATE
 1200 mg/30 mL
INACTIVE INGREDIENTS: WATER

HIGHLIGHTS OF PRESCRIBING INFORMATION

These highlights do not include all the information needed to use TOBRAMYCIN for injection safely and effectively. See full prescribing information for TOBRAMYCIN for injection.
TOBRAMYCIN for Injection, for intravenous use
Initial U.S. Approval: 1975

RECENT MAJOR CHANGES

Warnings and Precautions, Ototoxicity (5.2) | 2/2023

WARNING: NEPHROTOXICITY, OTOTOXICITY AND EMBRYO-FETAL TOXICITY

WARNING: NEPHROTOXICITY, OTOTOXICITY, NEURO MUSCULAR BLOCKADE AND FETAL HARM

See full prescribing information for complete boxed warning.

Nephrotoxicity

Tobramycin for Injection may cause acute kidney injury. Monitor renal function and serum tobramycin concentrations in all patients. Reduce the dose or discontinue the Tobramycin for Injection if renal impairment occurs. (5.1)

Ototoxicity

Tobramycin for Injection may cause irreversible auditory and vestibular toxicity. Monitor for symptoms of ototoxicity, and for renal function and serum tobramycin levels in all patients. Reduce the dose or discontinue the Tobramycin for Injection if impairment of renal function occurs. Discontinue Tobramycin for Injection if ototoxicity occurs. (5.2)

Neuromuscular Blockade

Aminoglycosides have been associated with neuromuscular blockade. During therapy with Tobramycin for Injection, monitor for adverse reactions associated with neuromuscular blockade, particularly in high-risk patients (5.5)

Embryo-Fetal Toxicity

Tobramycin for Injection and other aminoglycosides can cause fetal harm when administered to a pregnant woman. Apprise pregnant women of the potential hazard to the fetus. (5.3, 8.1)

1 INDICATIONS AND USAGE

Tobramycin for Injection, is an aminoglycoside antibacterial indicated for the treatment of serious bacterial infections caused by susceptible isolates of the designated bacteria in the diseases listed below (1.1):

- Septicemia in the pediatric patient and adults caused by P. aeruginosa, E. coli, and Klebsiella species (spp).
- Lower respiratory tract infections caused by P. aeruginosa, Klebsiella spp, Enterobacter spp, Serratia spp, E. coli, and S. aureus
- Serious central nervous system infections (meningitis) caused by susceptible organisms.
- Intra-abdominal infections, including peritonitis, caused by E. coli, Klebsiella spp., and Enterobacter spp.
- Skin, bone, and skin structure infections caused by P. aeruginosa, Proteus spp, E. coli, Klebsiella spp., Enterobacter spp., and S. aureus. Complicated urinary tract infections caused by P. aeruginosa, Proteus spp., (indole-positive and indole-negative), E. coli, Klebsiella spp.,

Enterobacter spp., Serratia spp., S. aureus, Providencia spp., and Citrobacter spp.

To reduce the development of drug-resistant bacteria and maintain the effectiveness of Tobramycin for Injection and other antibacterial drugs, Tobramycin for Injection should be used only to treat or prevent infections that are proven or strongly suspected to be caused by bacteria (1.2).

2 DOSAGE AND ADMINISTRATION

PHARMACY BULK PACKAGE-Not for Direct Infusion: Dispense single doses to many patients in a pharmacy admixture program. Pharmacy bulk package vial must be reconstituted and diluted prior to intravenous administration (2.1, 2.8)

Recommended adult dosages are as follows:

- Serious Infections: Administer 3 mg/kg/day in 3 equal doses (i.e. 1 mg/kg every 8 hours)
- Life-threatening Infections: Administer up to 5 mg/kg in 3 or 4 equal doses
- See full prescribing information for the recommended dosage for pediatric patients (2.3), patients with cystic fibrosis (2.5), patients with renal impairment (2.6), and obese patients (2.7).

3 DOSAGE FORMS AND STRENGTHS

Tobramycin for Injection, USP is supplied as a dry powder in a bulk package vial. Reconstitute the contents of the vial with 30 mL of Sterile Water for Injection, USP, to provide a solution containing 40 mg of tobramycin per mL (3).

4 CONTRAINDICATIONS

A history of hypersensitivity or serious toxic reactions to any aminoglycoside (4).

5 WARNINGS AND PRECAUTIONS

- Nephrotoxicity and ototoxicity: See Boxed Warning (5.1, 5.2)
- Allergic Reactions: anaphylaxis, exfoliative dermatitis, toxic epidermal necrolysis, erythema multiforme, and Stevens-Johnson Syndrome have been reported in patients on Tobramycin for Injection therapy. If an allergic reaction occurs, discontinue the drug and institute appropriate therapy (5.4)
- Neuromuscular Blockade: Respiratory paralysis can occur at high doses or with concurrent use of neuromuscular blocking agents. If neuromuscular blockade occurs, consider administration of calcium salts but mechanical assistance may be necessary. (5.5)
- Clostridioides difficile-associated diarrhea (CDAD): Evaluate patients if diarrhea occurs. (5.6)

6 ADVERSE REACTIONS

Most common adverse reactions are ototoxicity and nephrotoxicity. (6)

To report SUSPECTED ADVERSE REACTIONS, contact Fresenius Kabi USA, LLC at 1-800-551-7176 or FDA at 1-800-FDA-1088 or www.fda.gov/medwatch.

FULL PRESCRIBING INFORMATION

WARNING: NEPHROTOXICITY, OTOTOXICITY AND EMBRYO-FETAL TOXICITY

Nephrotoxicity

Tobramycin for Injection can result in acute kidney injury, including acute renal failure. Risk factors that may contribute to nephrotoxicity include tobramycin accumulation (increasing serum trough levels), high peak concentrations (above 12 mcg/mL), total cumulative dose, advanced age, volume depletion and concurrent or sequential use of other nephrotoxic drugs. Avoid concurrent or sequential use of other potentially nephrotoxic drugs. Monitor serum tobramycin levels and renal function in all patients during drug treatment. Reduce the dose or discontinue the Tobramycin for Injection if renal impairment occurs [see Warnings and Precautions (5.1)].

Ototoxicity

Tobramycin for Injection can cause irreversible auditory and vestibular toxicity that may continue to develop after the drug has been discontinued. Risk factors include high serum concentrations, prolonged therapy, renal impairment, concurrent and sequential use of other nephrotoxic or ototoxic drugs (e.g. aminoglycosides), and extremes of age. Avoid concurrent or sequential use with other potentially ototoxic drugs. Monitor for signs and symptoms of auditory and vestibular toxicity. Reduce the dose or discontinue the Tobramycin for Injection if renal impairment occurs. Discontinue the Tobramycin for Injection if ototoxicity occurs. [see Warnings and Precautions (5.2)].

Neuromuscular Blockade

Aminoglycosides have been associated with neuromuscular blockade. During therapy with Tobramycin for Injection, monitor for adverse reactions associated with neuromuscular blockade, particularly in high-risk patients, such as patients with underlying neuromuscular disorders (including myasthenia gravis) or in patients concomitantly receiving neuromuscular blocking agents [see Warnings and Precautions (5.5)].

Embryo-Fetal Toxicity

Tobramycin and other aminoglycosides can cause fetal harm when administered to a pregnant woman. If Tobramycin for Injection is used during pregnancy or if the patient becomes pregnant while taking tobramycin, apprise the patient of the potential hazard to the fetus [see Warnings and Precautions (5.3) and Use in Specific Populations (8.1)].

1 INDICATIONS AND USAGE

1.1 Septicemia

Tobramycin for Injection is indicated for the treatment of septicemia caused by susceptible isolates of P. aeruginosa, E. coli, and Klebsiella spp., in adult and pediatric patients.

1.2 Lower Respiratory Tract Infections

Tobramycin for Injection is indicated for the treatment of lower respiratory tract infections caused by susceptible isolates of P. aeruginosa, Klebsiella spp., Enterobacter spp., Serratia spp., E. coli, and S. aureus in adult and pediatric patients.

1.3 Central Nervous System Infections (Meningitis)

Tobramycin for Injection is indicated for the treatment of bacterial meningitis caused by susceptible bacteria in adult and pediatric patients.

1.4 Intra-abdominal Infections

Tobramycin for Injection is indicated for the treatment of intra-abdominal infections, including peritonitis, caused by susceptible isolates of E. coli, Klebsiella spp., and Enterobacter spp. in adult and pediatric patients.

1.5 Skin and Skin Structure Infections

Tobramycin for Injection is indicated for the treatment of skin and skin structure infections caused by susceptible isolates of P. aeruginosa, Proteus spp., E. coli, Klebsiella spp., Enterobacter spp., and S. aureus in adult and pediatric patients.

1.6 Bone Infections

Tobramycin for Injection is indicated for the treatment of bone infections caused by susceptible isolates of P. aeruginosa, Proteus spp., E. coli, Klebsiella spp., Enterobacter spp., and S. aureus in adult and pediatric patients

1.7 Complicated and Recurrent Urinary Tract Infections

Tobramycin for Injection is indicated for the treatment of complicated urinary tract infections caused by susceptible isolates of P. aeruginosa, Proteus spp., (indole-positive and indole-negative), E. coli, Klebsiella spp., Enterobacter spp., Serratia spp., S. aureus, Providencia spp., and Citrobacter spp. in adult and pediatric patients

1.8 Usage

To reduce the development of drug-resistant bacteria and maintain the effectiveness of Tobramycin for Injection and other antibacterial drugs, Tobramycin for Injection should be used only to treat or prevent infections that are proven or strongly suspected to be caused by susceptible bacteria. When culture and susceptibility information are available, they should be considered in selecting or modifying antibacterial therapy. In the absence of such data, local epidemiology and susceptibility patterns may contribute to the empiric selection of therapy.

2 DOSAGE AND ADMINISTRATION

2.1 Important Preparation and Administration Instructions

Pharmacy Bulk Package-Not for Direct Infusion

Tobramycin for Injection Pharmacy Bulk Package is intended for dispensing of single doses to many patients in a hospital pharmacy admixture service. It should only be prepared in an aseptic work area, such as a laminar flow hood. Tobramycin for Injection Pharmacy Bulk Package vial must be reconstituted and diluted prior to intravenous administration [see Dosage and Administration (2.8)]. After reconstitution, the closure may be penetrated only one time using a suitable sterile transfer device or dispensing set, which allows measured dispensing of the contents. Use of a syringe and needle is not recommended as it may cause leakage. After penetration, the entire contents of the bulk vial must be dispensed within 24 hours. Do not administer Tobramycin for Injection as a direct, undiluted intravenous injection.

2.2 Dosage for Adult Patients with Normal Renal Function

Tobramycin for Injection may be given intramuscularly or intravenously. Recommended dosages are the same for both routes. The recommended dosage is as follows:

Adult Patients

Adults with Serious Infections

3 mg/kg/day administered in 3 equal doses of 1 mg/kg every 8 hours.

Adults with Life-Threatening Infections

Up to 5 mg/kg/day may be administered in 3 or 4 equal doses (see Table 1). The dosage should be reduced to 3 mg/kg/day as soon as clinically indicated. To prevent increased toxicity due to excessive serum concentrations, dosage should not exceed 5 mg/kg/day unless serum concentrations are monitored [see Boxed Warning, Warnings and Precautions (5.2)].

Table 1 DOSAGE SCHEDULE GUIDE FOR ADULTS WITH NORMAL RENAL FUNCTION (Dosage at 8-Hour Intervals)
For Patient Weighing |  | Usual Dose for Serious Infections 1 mg/kg Every 8 hours (h)
kg | lb | (Total, 3 mg/kg/day)
 |  | mg/dose | mL/dose*
 |  | q8h
120 | 264 | 120 mg | 3 mL
115 | 253 | 115 mg | 2.9 mL
110 | 242 | 110 mg | 2.75 mL
105 | 231 | 105 mg | 2.6 mL
100 | 220 | 100 mg | 2.5 mL
95 | 209 | 95 mg | 2.4 mL
90 | 198 | 90 mg | 2.25 mL
85 | 187 | 85 mg | 2.1 mL
80 | 176 | 80 mg | 2 mL
75 | 165 | 75 mg | 1.9 mL
70 | 154 | 70 mg | 1.75 mL
65 | 143 | 65 mg | 1.6 mL
60 | 132 | 60 mg | 1.5 mL
55 | 121 | 55 mg | 1.4 mL
50 | 110 | 50 mg | 1.25 mL
45 | 99 | 45 mg | 1.1 mL
40 | 88 | 40 mg | 1 mL

For Patient Weighing |  |  | Maximum Dose for Life- Threatening Infections (Reduce as soon as possible) 1.66 mg/kg Every 8 hours
kg | lb |  | (Total, 5 mg/kg/day)
 |  |  | mg/dose |  | mL/dose*
 |  |  | Every 8h
120 |  | 264 | 200 mg |  | 5 mL
115 |  | 253 | 191 mg |  | 4.75 mL
110 |  | 242 | 183 mg |  | 4.5 mL
105 |  | 231 | 175 mg |  | 4.4 mL
100 |  | 220 | 166 mg |  | 4.2 mL
95 |  | 209 | 158 mg |  | 4 mL
90 |  | 198 | 150 mg |  | 3.75 mL
85 |  | 187 | 141 mg |  | 3.5 mL
80 |  | 176 | 133 mg |  | 3.3 mL
75 |  | 165 | 125 mg |  | 3.1 mL
70 |  | 154 | 116 mg |  | 2.9 mL
65 |  | 143 | 108 mg |  | 2.7 mL
60 |  | 132 | 100 mg |  | 2.5 mL
55 |  | 121 | 91 mg |  | 2.25 mL
50 |  | 110 | 83 mg |  | 2.1 mL
45 |  | 99 | 75 mg |  | 1.9 mL
40 |  | 88 | 66 mg |  | 1.6 mL
*Applicable to all product forms except the Tobramycin Injection, USP, (Pediatric).

2.3 Dosage for Pediatric Patients

Pediatric Patients (Greater than 1 Week of Age):

6 to 7.5 mg/kg/day administered in 3 or 4 equally divided doses (2 to 2.5 mg/kg every 8 hours or 1.5 to 1.9 mg/kg every 6 hours).

Premature or Full-Term Neonates (1 Week of Age or Less):

Up to 4 mg/kg/day may be administered in 2 equal doses every 12 hours.

2.4 Duration of Treatment for Adult and Pediatric Patients

The usual duration of treatment for adult and pediatric patients is 7 to10 days. A longer course of therapy may be necessary in complicated infections. In such cases, monitoring of renal, auditory, and vestibular functions is advised, because neurotoxicity is more likely to occur when treatment is extended longer than 10 days.

2.5 Dosage in Patients with Cystic Fibrosis or Burns

In patients with cystic fibrosis, altered pharmacokinetics may result in reduced serum concentrations of aminoglycosides. An initial dosing regimen of 10 mg/kg/day in 4 equally divided doses is suggested as a guide. The serum concentrations of tobramycin should be monitored during treatment due to wide inter-patient variability.

Similarly, altered pharmacokinetics may result in reduced serum concentrations in patients with extensive burns. Monitoring tobramycin serum concentration in these patients is especially important as a basis for determination of appropriate dosage [see Dosage and Administration (2.9)].

2.6 Dosage for Patients with Renal Impairment

Following a loading dose of 1 mg/kg, subsequent dosage in these patients must be adjusted, either with reduced doses administered at 8-hour intervals or with normal doses given at prolonged intervals. Both of these methods are suggested as guides and dose should be adjusted based on serum concentration. The dosage adjustment for patients with renal impairment are based on either the creatinine clearance level or the serum creatinine level of the patient because these values correlate with the half-life of tobramycin. The dosage schedule derived from either method should be used in conjunction with careful clinical and laboratory observations of the patient and serum tobramycin concentration monitoring and should be modified as necessary. Neither method should be used when dialysis is being performed.

Reduced dosage at 8-hour intervals

When the creatinine clearance rate is less than or equal to 70 mL per minute or when the serum creatinine value is known, the amount of the reduced dose can be determined by multiplying the normal dose in adult patients from Table 1 by the percent of the normal dosage from the accompanying nomogram in Figure 1 below.

Figure 1: NOMOGRAM

Normal dosage at prolonged intervals

If the creatinine clearance rate is not available and the patient's condition is stable, a dosage frequency in hours for the recommended adult dose can be determined by multiplying the patient's serum creatinine by 6.

2.7 Dosage in Obese Patients

The appropriate dose may be calculated by using the patient's estimated lean body weight plus 40% of the excess as the weight on which to determine the dose in mg/kg.

2.8 Instructions for Preparation and Intravenous Administration

Tobramycin for Injection is supplied as a dry powder in a pharmacy bulk package vial that

contains the equivalent of 1.2 g of tobramycin. The contents of the vial must be reconstituted and diluted prior to intravenous administration as follows:

- Reconstitute the contents of the pharmacy bulk package vial aseptically with 30 mL of Sterile Water for Injection, USP to provide a reconstituted solution containing 40 mg of tobramycin per mL.
- Dilute the reconstituted pharmacy bulk vial prior to intravenous administration by adding a specified volume of the reconstituted solution to 50 to 100 mL (for adult doses) of diluent (0.9% Sodium Chloride Injection or 5% Dextrose Injection) for each patient. For pediatric patients, the volume of diluent should be proportionately less than for adults.
- After penetration, entire contents of pharmacy bulk vial should be dispensed within 24 hours.
- Visually inspect for particulate matter and discoloration prior to administration The diluted solution should be intravenously infused over a period of 20 to 60 minutes. Intravenous infusion periods of less than 20 minutes are not recommended because peak serum concentrations may exceed 12 mcg/mL [see Dosage and Administration (2.9)].

2.9 Measurement of Serum Concentrations of Tobramycin

Measure peak and trough serum tobramycin concentrations periodically during therapy to assure adequate concentrations and to avoid potentially toxic concentrations in all patients, especially in patients with renal impairment [see Dosage and Administration (2.6)]. Avoid peak serum concentrations above 12 mcg/mL. Rising trough concentrations (above 2 mcg/mL) may indicate tissue accumulation. Such accumulation may result in ototoxicity and nephrotoxicity [Warnings and Precautions (5.1, 5.2)].

A useful guideline is to measure serum concentrations after 2 or 3 doses, so that the dosage could be adjusted if necessary, and at 3- to 4-day intervals during therapy. In the event of changing renal function, obtain more frequent serum tobramycin concentrations and adjust the dosage or dosage interval according to the guidelines provided [see Dosage and Administration (2.6)].

In order to measure the peak concentration, a serum sample should be drawn about 30 minutes following intravenous infusion or 1 hour after an intramuscular injection. Trough concentrations are measured by obtaining serum samples at 8 hours or just prior to the next dose of tobramycin. These suggested time intervals are intended only as guidelines and may vary according to institutional practices. It is important, however, that there be consistency within the individual patient program unless computerized pharmacokinetic dosing programs are available in the institution. These serum-concentration assays may be especially useful for monitoring the treatment of severely ill patients with changing renal function or of those infected with less susceptible organisms or those receiving maximum dosage.

2.10 Drug Incompatibilities

Tobramycin should not be physically premixed with other drugs but should be administered separately according to the recommended dose and route.

3 DOSAGE FORMS AND STRENGTHS

Tobramycin for Injection, USP is supplied as a sterile dry powder in a pharmacy bulk package vial containing tobramycin sulfate equivalent to 1.2 g of tobramycin. The contents of the vial should be diluted with 30 mL of Sterile Water for Injection, USP, to provide a solution containing 40 mg of tobramycin per mL.

4 CONTRAINDICATIONS

Tobramycin for Injection is contraindicated in patients with a history of hypersensitivity to tobramycin or any other aminoglycoside [see Warnings and Precautions (5.4)].

5 WARNINGS AND PRECAUTIONS

5.1 Nephrotoxicity

Systemic exposure to Tobramycin for Injection and other aminoglycosides can cause nephrotoxicity, primarily manifested as acute tubular necrosis. Signs of nephrotoxicity include rising blood urea nitrogen (BUN) and creatinine (Cr), decreased urinary output, and sodium, potassium, bicarbonate, magnesium, phosphate and calcium urinary losses. Aminoglycoside-induced nephrotoxicity may occur during therapy but may not become apparent until the first few days after cessation of therapy and usually is reversible. The risk for nephrotoxicity increases with tobramycin accumulation (indicated by rising trough levels above 2 mcg/mL), excessive peak concentrations (above 12 mcg/mL), total cumulative dose, advanced age, volume depletion, concurrent or sequential use of other nephrotoxic drugs and in patients with diabetes. Monitor serum tobramycin concentrations in all patients and avoid peak levels above 12 mcg/mL and trough levels above 2 mcg/mL [see Dosage and Administration (2.9)]. Monitor renal function, serum electrolytes, potassium, sodium, magnesium, calcium and phosphate, urine output and urinalysis during therapy in all patients. Reduce the dose or discontinue treatment if renal impairment occurs.

5.2 Ototoxicity

Ototoxicity with use of Tobramycin for Injection

Tobramycin for Injection can cause both auditory and vestibular eighth nerve damage. The auditory changes are irreversible, are usually bilateral, and may be partial or total. Symptoms of ototoxicity can include dizziness, vertigo, tinnitus, roaring in the ears and hearing loss. Ototoxicity symptoms may manifest during therapy or after tobramycin has been discontinued. The risk of ototoxicity increases with higher peak and trough serum tobramycin concentrations, in patients who receive high doses or prolonged or prior treatment with tobramycin or other aminoglycosides, in patients with renal impairment, patients receiving with other nephrotoxic or ototoxic drugs and in the extremes of age. To decrease the risk of ototoxicity, use as short a duration of therapy as clinically appropriate, adequately hydrate patients, limit the use of other ototoxic drugs, and closely monitor tobramycin concentrations during therapy [see Dosage and Administration (2.9)]. Monitor patients for signs and symptoms of auditory or vestibular toxicity and consider serial audiograms in high-risk patients. Discontinue tobramycin in patients with evidence of auditory or vestibular toxicity.

Risk of Ototoxicity Due to Mitochondrial DNA Variants

Cases of ototoxicity with aminoglycosides have been observed in patients with certain variants in the mitochondrially encoded 12S rRNA gene (MT-RNR1), particularly the m.1555A>G variant. Ototoxicity occurred in some patients even when their aminoglycoside serum levels were within the recommended range. Mitochondrial DNA variants are present in less than 1% of the general US population, and the proportion of the variant carriers who may develop ototoxicity as well as the severity of ototoxicity is unknown. In case of known maternal history of ototoxicity due to aminoglycoside use or a known mitochondrial DNA variant in the patient, consider alternative treatments other than aminoglycosides unless the increased risk of permanent hearing loss is outweighed by the severity of infection and lack of safe and effective alternative therapies.

5.3 Embryo-Fetal Toxicity

Aminoglycosides, including Tobramycin for Injection, can cause fetal harm when administered to a pregnant woman. Aminoglycosides cross the placenta. Streptomycin, another aminoglycoside, has been associated with several reports of total, irreversible, bilateral congenital deafness in pediatric patients whose mothers received streptomycin during pregnancy. Apprise patients of potential hazard to the fetus if Tobramycin for Injection is used during pregnancy or if the patient becomes pregnant while taking Tobramycin for Injection [see Use in Specific Populations (8.1)].

5.4 Allergic Reactions

Serious and fatal allergic reactions including anaphylaxis and dermatologic reactions including exfoliative dermatitis, toxic epidermal necrolysis, erythema multiforme, and Stevens-Johnson Syndrome have been reported in patients on tobramycin therapy [see Contraindications (4) and Adverse Reactions (6)].

If an allergic reaction occurs, discontinue Tobramycin for Injection and institute appropriate therapy. A history of hypersensitivity to other aminoglycosides is a contraindication to the use of Tobramycin for Injection, because cross-allergenicity among aminoglycosides has been demonstrated [see Contraindications (4)].

5.5 Neuromuscular Blockade and Other Neurologic Adverse Reactions

Neuromuscular blockade with respiratory paralysis and respiratory failure may occur following administration of aminoglycosides. Neuromuscular blockade, respiratory failure, and prolonged respiratory paralysis may occur more commonly and be more severe in patients with myasthenia gravis or Parkinson's disease and in patients concomitantly receiving neuromuscular blocking agents such as succinylcholine. If neuromuscular blockade occurs following the administration of Tobramycin for Injection, it may be reversed by the administration of calcium salts but mechanical assistance may be necessary. Other manifestations of neurotoxicity may include numbness, skin tingling, muscle twitching, and convulsions.

5.6 Clostridioides difficile-Associated Diarrhea (CDAD)

Clostridioides difficile-associated diarrhea (CDAD) has been reported with use of nearly all antibacterial agents, including Tobramycin for Injection, USP, and may range in severity from mild diarrhea to fatal colitis. Treatment with antibacterial agents alters the normal flora of the colon leading to overgrowth of C. difficile.

C. difficile produces toxins A and B which contribute to the development of CDAD. Hypertoxin producing strains of C. difficile cause increased morbidity and mortality, as these infections can be refractory to antibacterial therapy and may require colectomy. CDAD must be considered in all patients who present with diarrhea following antibacterial use. Careful medical history is necessary since CDAD has been reported to occur over two months after the administration of antibacterial agents.

If CDAD is suspected or confirmed, ongoing antibacterial use not directed against C. difficile may need to be discontinued. Appropriate fluid and electrolyte management, protein supplementation, antibacterial treatment of C. difficile, and surgical evaluation should be instituted as clinically indicated.

5.7 Risk of Development of Drug-Resistant Bacteria

Prescribing Tobramycin for Injection, USP in the absence of a proven or strongly suspected bacterial infection is unlikely to provide benefit to the patient and increases the risk of the development of drug-resistant bacteria.

5.8 Macular Necrosis

Tobramycin for Injection is not approved for intraocular and/or subconjunctival use. Macular necrosis has been reported following intraocular and/ or subconjunctival administration of aminoglycosides, including tobramycin.

5.9 Inactivation by Beta-Lactam Antibacterials

The inactivation of tobramycin and other aminoglycosides by ß-lactam-type antibacterials (penicillins, cephalosporins) has been demonstrated in vitro and in patients with severe renal impairment. Such inactivation has not been found in patients with normal renal function who have been given the drugs by separate routes of administration.

6 ADVERSE REACTIONS

The following serious adverse reactions are described below and elsewhere in the labeling:

- Nephrotoxicity [see Boxed Warning and Warnings and Precautions (5.1)]
- Ototoxicity [see Boxed Warning and Warnings and Precautions (5.2)]
- Embryo-Fetal Toxicity [see Boxed Warning and Warnings and Precautions (5.3)]
- Allergic Reactions [see Warnings and Precautions (5.4)]
- Neuromuscular Blockade [see Warnings and Precautions (5.5)]

The following adverse reactions associated with the use of Tobramycin for Injection were identified in clinical studies or postmarketing reports. Because some of these reactions were reported voluntarily from a population of uncertain size, it is not always possible to reliably estimate their frequency or establish a causal relationship to drug exposure.

Blood and Lymphatic System Disorders: anemia, granulocytopenia, leukopenia, leukocytosis, eosinophilia and thrombocytopenia

Ear and Labyrinth Disorders: Tinnitus, hearing loss, vertigo

Gastrointestinal Disorders: nausea, vomiting, diarrhea

General Disorders and Administration Site Conditions: fever, lethargy, pain at the injection site

Immune system disorders: Anaphylaxis, hypersensitivity reactions

Laboratory Investigations: elevated blood urea nitrogen, elevated serum creatinine, hyponatremia, hypokalemia, hypomagnesemia, hypocalcemia, hypophosphatemia, urinary casts, increased serum transaminases (AST, ALT); increased serum LDH and bilirubin

Nervous System Disorders: headache, numbness, paresthesia, muscle twitching, convulsions, mental confusion, and disorientation

Skin and Subcutaneous Tissue Disorders: rash, itching, urticaria

7 DRUG INTERACTIONS

7.1 Drugs with Nephrotoxic or Ototoxic Potential

Avoid concurrent and/or sequential use of Tobramycin for Injection with other drugs with nephrotoxic and/or ototoxic potential.

7.2 Diuretics

Some diuretics can enhance aminoglycoside toxicity by altering concentrations in serum and tissue and causing dehydration. Monitor serum concentrations, renal function, serum electrolytes, sodium, magnesium, calcium and phosphate, urine output and urinalysis, and signs of auditory or vestibular toxicity in patients concomitantly administered diuretics.

7.3 Drugs with Neuromuscular Blockade or Neurotoxic Potential

Prolonged respiratory paralysis may occur in patients concomitantly receiving neuromuscular blocking agents with Tobramycin for Injection [see Boxed Warning, Warnings and Precautions (5.5)]. If neuromuscular blockade occurs, it may be reversed by the administration of calcium salts but mechanical assistance may be necessary. In addition, avoid concurrent and/or sequential use of Tobramycin for Injection with other neurotoxic drugs.

8 USE IN SPECIFIC POPULATIONS

8.1 Pregnancy

Risk Summary

Aminoglycosides, including Tobramycin for Injection, can cause fetal harm when administered to a pregnant woman. Published literature reports that use of streptomycin, an aminoglycoside, can cause total, irreversible, bilateral congenital deafness when administered to a pregnant woman [see Warnings and Precautions (5.3)]. In animal reproduction studies with subcutaneous administration of tobramycin in pregnant rats and rabbits during organogenesis, there were no adverse developmental outcomes at doses up to 3.2 times and 1.3 times the maximum recommended clinical dose based on body surface area; however, ototoxicity was not evaluated in the offspring from these studies (see Data). Advise pregnant women of the potential risk to a fetus.

The estimated background risk of major birth defects and miscarriage for the indicated populations are unknown. All pregnancies have a background risk of birth defects, loss, or other adverse outcomes. In the U.S. general population, the estimated background risk of major birth defects and miscarriage in clinically recognized pregnancies is 2 to 4% and 15 to 20% respectively.

Data

Animal Data

Subcutaneous administration of tobramycin at doses of up to 100 mg/kg/day (rat) or 20 mg/kg/day (rabbit) during organogenesis was not associated with adverse developmental outcomes. These doses are 3.2 and 1.3 times the maximum recommended clinical daily dose of 5 mg/kg based on body surface area. Doses of tobramycin ≥40 mg/kg/day were maternally toxic to rabbits and precluded the evaluation of adverse developmental outcomes. Ototoxicity was not evaluated in offspring during nonclinical reproductive toxicity studies with tobramycin.

8.2 Lactation

Risk Summary

Limited published data with Tobramycin for Injection in lactating women indicate that tobramycin is present in human milk. There are no data on the effects of Tobramycin for Injection on milk production. Tobramycin may cause alteration in the intestinal flora of the breastfeeding infant. Advise a woman to monitor the breastfed infant for loose or bloody stools and candidiasis (thrush, diaper rash).

The developmental and health benefits of breastfeeding should be considered along with the mother's clinical need for Tobramycin for Injection and any potential adverse effects on the breastfed infant from Tobramycin for Injection or from the underlying maternal condition.

8.4 Pediatric Use

Use Tobramycin for Injection with caution in premature infants and neonates because of their renal immaturity and the resulting prolongation of serum half-life. For pediatric dosing information [see Dosage and Administration (2.3)]. Similar to adults, monitor renal function and serum tobramycin concentrations in pediatric patients receiving Tobramycin for Injection.

8.5 Geriatric Use

Elderly patients may be at a higher risk of developing nephrotoxicity and ototoxicity while receiving Tobramycin for Injection [see Warnings and Precautions (5.1)].

Tobramycin is known to be substantially excreted by the kidney, and the risk of adverse reactions to this drug may be greater in patients with impaired renal function. Because elderly patients are more likely to have decreased renal function, care should be taken in dose selection, and it may be useful to monitor renal function and serum tobramycin levels [see Dosage and Administration (2.6) and Warnings and Precautions (5.1)].

8.6 Patients with Renal Impairment

The dosage schedule of Tobramycin for Injection should be adjusted according to the degree of renal impairment and serum concentration [see Dosage and Administration (2.6)]. In patients undergoing hemodialysis, 25% to 70% of the administered dose may be removed, depending on the duration and type of dialysis.

10 OVERDOSAGE

10.1 Signs and Symptoms

Acute overdosage with Tobramycin for Injection can result in more severe manifestations of the types of toxicities known to occur with recommended doses, e.g., renal damage, ototoxicity, neuromuscular blockade. The severity of the signs and symptoms following a tobramycin overdose are dependent on the dose administered, the patient's renal function, state of hydration, age and whether or not other medications with similar toxicities are being administered concurrently. [see Warnings and Precautions (5.1, 5.2, 5.5)] for signs and symptoms related to neurotoxicity, nephrotoxicity and neuromuscular blockade; and Adverse Reactions (6)].

If tobramycin were ingested, toxicity would be less likely because aminoglycosides are minimally absorbed from an intact gastrointestinal tract.

10.2 Treatment

In all cases of suspected overdosage with Tobramycin for Injection, call your Regional Poison Control Center or the National Poison Control center at 1-800-222-1222 or www.poison.org to obtain the most up-to-date information about the treatment of overdose. This recommendation is made because, in general, information regarding the treatment of overdosage may change more rapidly than the package insert.

Management of Tobramycin for Injection overdosage is symptomatic and supportive. Maintain airway, provide adequate hydration and monitor renal function, serum electrolytes, and tobramycin concentrations until the serum tobramycin level falls below 2 mcg/mL.

Tobramycin is removed by hemodialysis.

11 DESCRIPTION

Tobramycin sulfate, a water-soluble aminoglycoside antibacterial, drug derived from the actinomycete Streptomyces tenebrarius. Tobramycin for Injection, USP is supplied as a sterile powder in a pharmacy bulk package vial for intravenous use. It is intended for reconstitution with 30 mL of Sterile Water for Injection, USP. Each vial contains tobramycin sulfate equivalent to 1.2 g of tobramycin. After reconstitution, the solution will contain 40 mg of tobramycin per mL. The product contains no preservative or sodium bisulfite.

Tobramycin sulfate is O-3-amino-3-deoxy-α-D-glucopyranosyl-(1→4)-O-[2,6-diamino-2,3,6-trideoxy-α-D-ribo-hexopyranosyl-(1→6)]-2-deoxy-L-streptamine, sulfate (2:5)(salt) and has the molecular formula (C18H37N5O9)2•5H2SO4. The molecular weight is 1425.42 g/mol. The molecular weight of the free base is 467.51 g/mol. The structural formula of tobramycin, free base, is as follows:

Figure 2: Tobramycin Structure

12 CLINICAL PHARMACOLOGY

12.1 Mechanism of Action

Tobramycin sulfate is an aminoglycoside antibacterial drug [see Microbiology (12.4)].

12.3 Pharmacokinetics

In patients with normal renal function, except neonates, tobramycin administered every 8 hours does not accumulate in serum. The serum elimination half-life in patients with normal renal function is 2 hours. However, in patients with renal impairment and in neonates, serum concentrations of the antibacterial are usually higher and can be measured for longer periods of time than in adults with normal renal function. Thus, the dosage of Tobramycin for Injection for patients with renal impairment and neonates must be adjusted accordingly [see Dosage and Administration (2.3, 2.6)].

Absorption

Following intramuscular administration, peak serum concentrations of tobramycin occur between 30 and 90 minutes. Following an intramuscular dose of 1 mg/kg of body weight, maximum serum concentrations reach about 4 mcg/mL, and measurable concentrations persist for as long as 8 hours. Therapeutic serum concentrations are generally considered to range from 4 to 6 mcg/mL. When Tobramycin for Injection is administered by intravenous infusion over a 1-hour period, the serum concentrations are similar to those obtained by intramuscular administration. Tobramycin is poorly absorbed from the gastrointestinal tract.

Distribution

Based on ultrafiltration studies, practically no serum protein binding of tobramycin occurs.

Tobramycin can be detected in tissues and body fluids after parenteral administration. Concentrations of tobramycin in bile and stools ordinarily have been low, which suggests minimal biliary excretion. The concentration of tobramycin in cerebrospinal fluid following parenteral administration is low, and concentrations are dependent on dose, rate of penetration, and degree of meningeal inflammation. Tobramycin has also been detected in sputum, peritoneal fluid, synovial fluid, and abscess fluids, and it crosses the placental membranes. Concentrations in the renal cortex are several times higher than serum concentrations.

Metabolism

Following parenteral administration, minimal, metabolic transformation occurs, and tobramycin is eliminated almost exclusively by glomerular filtration.

Excretion

Peak urine concentrations ranging from 75 to 100 mcg/mL have been observed following the intramuscular injection of a single dose of 1 mg/kg. After several days of treatment, the amount of tobramycin excreted in the urine approaches the daily dose administered. Renal clearance is similar to that of endogenous creatinine. In patients with normal renal function, up to 84% of the dose is recoverable from the urine in 8 hours and up to 93% in 24 hours. When renal function is impaired, excretion of tobramycin is slowed, and accumulation of the drug may cause toxic blood concentrations.

Drug Interactions

Probenecid does not affect the renal tubular transport of tobramycin.

12.4 Microbiology

Mechanism of Action

Tobramycin is an aminoglycoside that inhibits protein synthesis by binding to the aminoacyl site (A) of the 16S RNA within the bacterial 30S ribosomal subunit. Tobramycin is bactericidal against susceptible bacteria.

Resistance

Resistance to aminoglycosides includes production of aminoglycoside modifying enzymes (AMEs), alteration of the ribosomal target through production of 16S rRNA methyltransferases, up-regulation of efflux pumps and reduced permeability into bacterial cell due to loss of outer membrane porins. Aminoglycosides are generally not active against most gram-positive organisms, including Streptococcus pyogenes, Streptococcus pneumoniae, and enterococci. Cross-resistance between aminoglycosides may occur.

Interaction with Other Antimicrobials

In vitro studies have shown that an aminoglycoside combined with an antibacterial that interferes with cell-wall synthesis, such as penicillin, results in a synergistic bactericidal effect in some isolates of Enterococcus faecalis. This combination is not synergistic against other closely related organisms, e.g., Enterococcus faecium. Species-level identification of enterococci alone cannot be used to predict susceptibility. Susceptibility testing and tests for antibacterial synergism must be performed.

Antimicrobial Activity

Tobramycin has been shown to be active against most isolates of the following bacteria both in vitro and in clinical infections [see Indications and Usage (1)]:

Gram-positive bacteria

Staphylococcus aureus

Gram-negative bacteria

Citrobacter species

Enterobacter species

Escherichia coli

Klebsiella species

Morganella morganii

Pseudomonas aeruginosa

Proteus mirabilis

Proteus vulgaris

Providencia species

Serratia species

Susceptibility Testing

For specific information regarding susceptibility test interpretive criteria and associated test methods and quality control standards recognized by FDA for this drug, please see: https://www.fda.gov/STIC.

13 NONCLINICAL TOXICOLOGY

13.1 Carcinogenesis, Mutagenesis, Impairment of Fertility

Carcinogenesis

Carcinogenicity studies in animals have not been conducted with Tobramycin for Injection.

Mutagenesis

Tobramycin has been evaluated for genotoxicity in a battery of in vitro and in vivo tests. The Ames bacterial reversion test, conducted with 5 tester strains, failed to show a significant increase in revertants with or without metabolic activation in all strains. Tobramycin was negative in the mouse lymphoma forward mutation assay, did not induce chromosomal aberrations in Chinese hamster ovary cells, and was negative in the mouse micronucleus test.

Impairment of Fertility

Subcutaneous administration of up to 100 mg/kg of tobramycin (3.2 times the maximum recommended clinical dose of 5 mg/kg/day based on body surface area) did not affect mating behavior or cause impairment of fertility in male or female rats.

16 HOW SUPPLIED/STORAGE AND HANDLING

16.1 How Supplied

Tobramycin for Injection, USP is supplied as a sterile dry powder containing tobramycin sulfate equivalent to 1.2 g tobramycin in a 50 mL Pharmacy Bulk Package Vial packaged in trays of 6.

Product Code | Unit of Sale | Strength | Each
NP300351 | NDC 63323-303-55 Unit of 6 | 1.2 g in 50 mL | NDC 63323-303-21 50 mL Pharmacy Bulk Package Vial

Vial stoppers do not contain natural rubber latex.

16.2 Storage and Handling

Prior to reconstitution, the vial should be stored at 20°C to 25°C (68°F to 77°F) [see USP Controlled Room Temperature]. After reconstitution, the solution should be kept in a refrigerator and used within 96 hours. If kept at room temperature, the solution must be used within 24 hours [see Dosage and Administration (2.1, 2.8)].

17 PATIENT COUNSELING INFORMATION

Serious Allergic Reactions

Advise patients that serious allergic reactions could occur with Tobramycin for Injection. Advise patients to report fever, swelling, difficulty breathing, wheezing, decrease blood pressure or dizziness, or skin rash. If an allergic reaction occurs, discontinue the drug and institute appropriate therapy immediately.

Impairment of Kidney Function

Advise patients that Tobramycin for Injection may cause impairment in kidney function and that periodic blood draws are required to monitor kidney function and tobramycin drug levels.

Hearing Loss and Impaired Balance

Advise patients that Tobramycin for Injection may cause serious and irreversible hearing loss and impaired balance. Advise patients to report hearing loss, ringing or roaring in the ears, dizziness or imbalance.

Antibacterial Resistance

Counsel patients that antibacterial drugs, including Tobramycin for Injection should be used to treat bacterial infections only. They do not treat viral infections (e.g., the common cold). When Tobramycin for Injection is prescribed to treat a bacterial infection, patients should be told that although it is common to feel better early in the course of therapy, the medication should be administered exactly as directed. Skipping doses or not completing the full course of therapy may (1) decrease the effectiveness of the immediate treatment and (2) increase the likelihood that bacteria will develop resistance and will not be treatable by Tobramycin for Injection or other antibacterial drugs in the future.

Diarrhea

Counsel patients that diarrhea is a common problem caused by antibacterials, and it usually ends when the antibacterial is discontinued. Sometimes after starting treatment with antibacterials, patients can develop watery and bloody stools (with or without stomach cramps and fever) even as late as 2 or more months after having taken their last dose of the antibacterial. If this occurs, patients should contact their physician as soon as possible.

Embryofetal Toxicity

Advise pregnant women that aminoglycosides, including Tobramycin for Injection, can cause irreversible congenital deafness when administered to a pregnant woman [see Warnings and Precautions (5.3) and Use in Specific Populations (8.1)].

Lactation

Advise a woman to monitor their breastfed infants for diarrhea and/or bloody stools [see Use in Specific Populations (8.2)].

Novaplus is a registered trademark of Vizient, Inc.

Manufactured by:
Fresenius Kabi
Lake Zurich, IL 60047

www.fresenius-kabi.com/us

451027D

PACKAGE LABEL

PACKAGE LABEL - PRINCIPAL DISPLAY - Tobramycin 1.2 g Vial Label

NDC 63323-303-21

NP300351

Tobramycin for Injection, USP

Equivalent to

1.2 g

Tobramycin

PHARMACY BULK PACKAGE - NOT FOR DIRECT INFUSION

Rx only

PACKAGE LABEL

PACKAGE LABEL - PRINCIPAL DISPLAY - Tobramycin 1.2 g Tray Label

NDC 63323-303-55

NP300351

Tobramycin for Injection, USP

Equivalent to

1.2 g

Tobramycin

PHARMACY BULK PACKAGE - NOT FOR DIRECT INFUSION

Rx only

6 x 50 mL pharmacy
bulk package vials